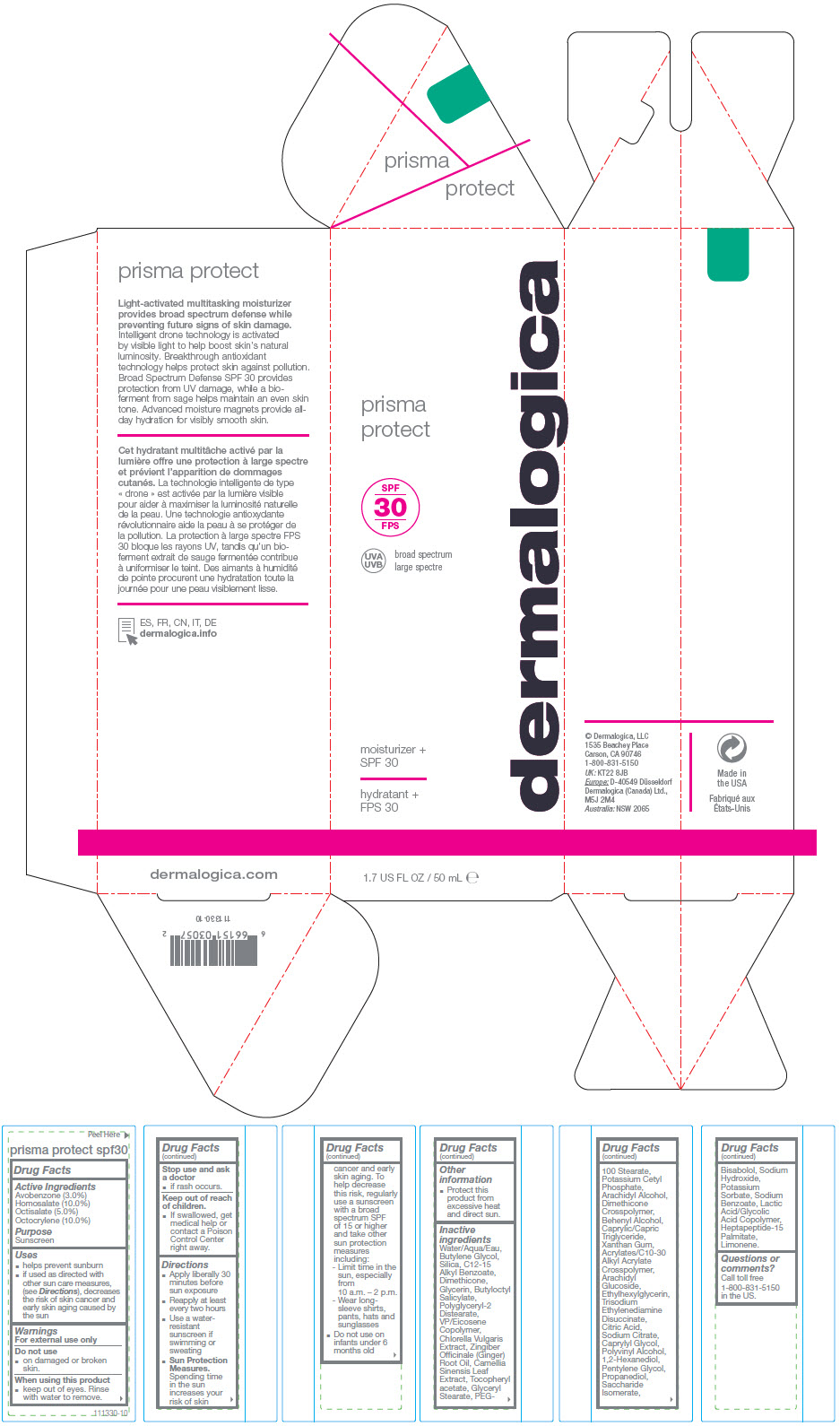 DRUG LABEL: PRISMA PROTECT SPF30
NDC: 68479-851 | Form: LOTION
Manufacturer: Dermalogica, LLC.
Category: otc | Type: HUMAN OTC DRUG LABEL
Date: 20241230

ACTIVE INGREDIENTS: Homosalate 10 g/100 mL; Octocrylene 10 g/100 mL; Octisalate 5 g/100 mL; Avobenzone 3 g/100 mL
INACTIVE INGREDIENTS: Water; Butylene Glycol; Silicon Dioxide; Alkyl (C12-15) Benzoate; Dimethicone; Glycerin; Butyloctyl Salicylate; Polyglyceryl-2 Distearate; Vinylpyrrolidone/Eicosene Copolymer; Potassium Cetyl Phosphate; Glyceryl Monostearate; PEG-100 Stearate; Pentylene Glycol; Propanediol; Arachidyl Alcohol; Saccharide Isomerate; Docosanol; Caprylyl Glycol; Medium-Chain Triglycerides; Xanthan Gum; Levomenol; Arachidyl Glucoside; Ethylhexylglycerin; .ALPHA.-TOCOPHEROL ACETATE, D-; Trisodium Ethylenediamine Disuccinate; Ginger Oil; Sodium Hydroxide; Green Tea Leaf; ANHYDROUS CITRIC ACID; 1,2-Hexanediol; Sodium Citrate, Unspecified Form; Potassium Sorbate; Sodium Benzoate; Chlorella Vulgaris; Polyvinyl Alcohol, Unspecified; Limonene, (+)-

PRISMA PROTECT SPF30

Drug Facts

Active Ingredients

Avobenzone (3.0%)
Homosalate (10.0%)
Octisalate (5.0%)
Octocrylene (10.0%)

Purpose

Sunscreen

Uses

- helps prevent sunburn
- if used as directed with other sun care measures, (see Directions), decreases the risk of skin cancer and early skin aging caused by the sun

Warnings

For external use only

Do not use

- on damaged or broken skin.

When using this product

- keep out of eyes. Rinse with water to remove.

Stop use and ask a doctor

- if rash occurs.

Keep out of reach of children.

- If swallowed, get medical help or contact a Poison Control Center right away.

Directions

- Apply liberally 30 minutes before sun exposure
- Reapply at least every two hours
- Use a water-resistant sunscreen if swimming or sweating
- Sun Protection Measures. Spending time in the sun increases your risk of skin cancer and early skin aging. To help decrease this risk, regularly use a sunscreen with a broad spectrum SPF of 15 or higher and take other sun protection measures including:
  - Limit time in the sun, especially from 10 a.m. – 2 p.m.
  - Wear long-sleeve shirts, pants, hats and sunglasses
- Do not use on infants under 6 months old

Other information

- Protect this product from excessive heat and direct sun.

Inactive ingredients

Water/Aqua/Eau, Butylene Glycol, Silica, C12-15 Alkyl Benzoate, Dimethicone, Glycerin, Butyloctyl Salicylate, Polyglyceryl-2 Distearate, VP/Eicosene Copolymer, Chlorella Vulgaris Extract, Zingiber Officinale (Ginger) Root Oil, Camellia Sinensis Leaf Extract, Tocopheryl acetate, Glyceryl Stearate, PEG-100 Stearate, Potassium Cetyl Phosphate, Arachidyl Alcohol, Dimethicone Crosspolymer, Behenyl Alcohol, Caprylic/Capric Triglyceride, Xanthan Gum, Acrylates/C10-30 Alkyl Acrylate Crosspolymer, Arachidyl Glucoside, Ethylhexylglycerin, Trisodium Ethylenediamine Disuccinate, Citric Acid, Sodium Citrate, Caprylyl Glycol, Polyvinyl Alcohol, 1,2-Hexanediol, Pentylene Glycol, Propanediol, Saccharide Isomerate, Bisabolol, Sodium Hydroxide, Potassium Sorbate, Sodium Benzoate, Lactic Acid/Glycolic Acid Copolymer, Heptapeptide-15 Palmitate, Limonene.

Questions or comments?

Call toll free 1-800-831-5150 in the US.

PRINCIPAL DISPLAY PANEL - 50 mL Tube Carton

prisma
protect

dermalogica

SPF
30

UVA
UVB

broad spectrum

moisturizer +
SPF 30

1.7 US FL OZ / 50 mL ℮